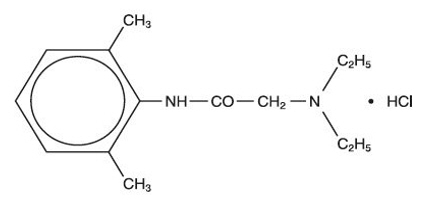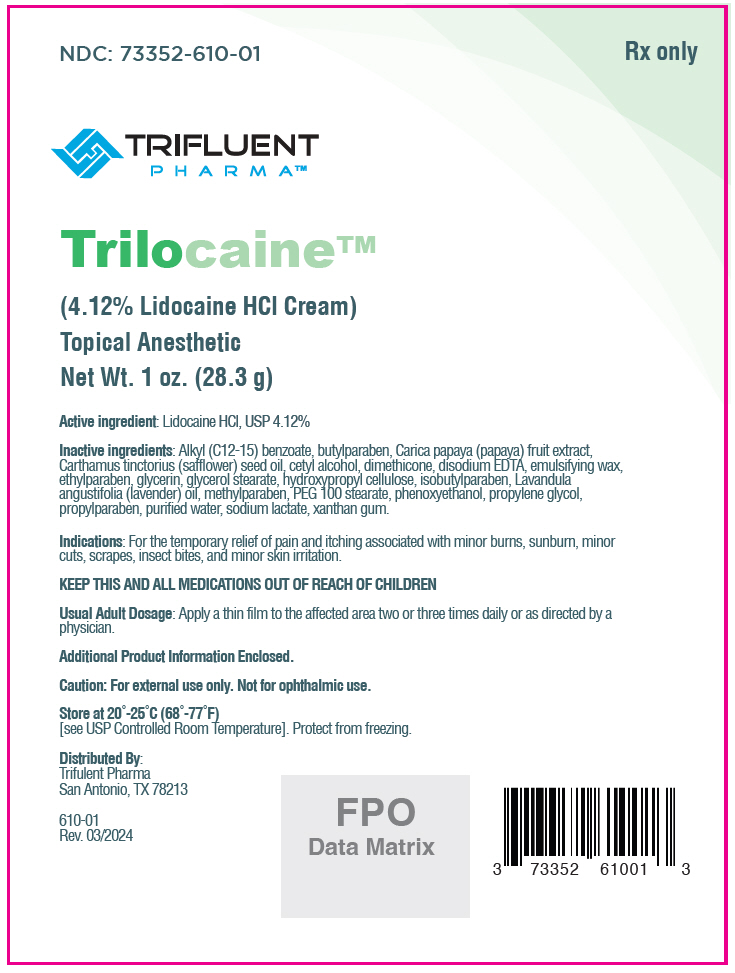 DRUG LABEL: Trilocaine
NDC: 73352-610 | Form: CREAM
Manufacturer: Trifluent Pharma LLC
Category: prescription | Type: HUMAN PRESCRIPTION DRUG LABEL
Date: 20251015

ACTIVE INGREDIENTS: LIDOCAINE HYDROCHLORIDE 41.2 mg/1 g
INACTIVE INGREDIENTS: ALKYL (C12-15) BENZOATE; BUTYLPARABEN; PAPAYA; SAFFLOWER OIL; CETYL ALCOHOL; DIMETHICONE, UNSPECIFIED; EDETATE DISODIUM; ETHYLPARABEN; GLYCERIN; GLYCERYL MONOSTEARATE; PEG-100 MONOSTEARATE; HYDROXYPROPYL CELLULOSE, UNSPECIFIED; ISOBUTYLPARABEN; LAVENDER OIL; METHYLPARABEN; PHENOXYETHANOL; PROPYLENE GLYCOL; PROPYLPARABEN; WATER; SODIUM LACTATE; XANTHAN GUM

Trilocaine™ 4.12% Cream
(Lidocaine HCl)
Topical Anesthetic

Rx only

Disclaimer: This drug has not been found by FDA to be safe and effective, and this labeling has not been approved by FDA. For further information about unapproved drugs, go to https://www.fda.gov/drugs/enforcement-activities-fda/unapproved-drugs

DESCRIPTION

Lidocaine hydrochloride has a chemical name of 2-(diethylamino)-N-(2,6-dimethylphenyl)acetamide;hydrochloride and has the molecular weight 270.8. Lidocaine hydrocholoride (C14H22N2O ∙ HCL) has the following structural formula:

Ingredients: Each gram of Trilocaine™ 4.12% Cream contains 41.2 mg Lidocaine HCl, USP.

Inactive Ingredients include: Alkyl (C12-15) benzoate, butylparaben, Carica papaya (papaya) fruit extract, Carthamus tinctorius (safflower) seed oil, cetyl alcohol, dimethicone, disodium EDTA, emulsifying wax, ethylparaben, glycerin, glycerol stearate, hydroxypropyl cellulose, isobutylparaben, Lavandula angustifolia (lavender) oil, methylparaben, PEG 100 stearate, phenoxyethanol, propylene glycol, propylparaben, purified water, sodium lactate, xanthan gum.

CLINICAL PHARMACOLOGY

Mechanism of Action

Trilocaine™ 4.12% Cream releases lidocaine to stabilize the neuronal membrane by inhibiting the ionic fluxes required for initiation and conduction of impulses, thereby effecting local anesthetic action.

Pharmacokinetics

Lidocaine may be absorbed following topical administration to mucous membranes; its rate and extent of absorption depending upon the specific site of application, duration of exposure, concentration, and total dosage. In general, the rate of absorption of local anesthetic agents following topical application occurs most rapidly after intratracheal administration. Lidocaine is also well-absorbed from the gastrointestinal tract, but little intact drug appears in the circulation because of biotransformation of the liver.

Lidocaine is metabolized rapidly by the liver, and metabolites and unchanged drug are excreted by the kidneys. Biotransformation includes oxidative N-dealkylation, ring hydroxylation, cleavage of the amide linkage, and conjugation. N-dealkylation, a major pathway of biotransformation, yields the metabolites monoethylglycinexylidide and glycinexlidide. The pharmacological/toxicological actions of these metabolites are similar to, but less potent than, those of lidocaine. Approximately 90% of lidocaine administered is excreted in the form of various metabolites and less than 10% is excreted unchanged. The primary metabolite in urine is a conjugate of 4-hydroxy-2, 6-dimethylaniline.

The plasma binding of lidocaine is dependent on drug concentration and the fraction bound decreases with increasing concentration. At concentration of 1 to 4 g of free base per mL, 60 to 80 percent of lidocaine is protein bound. Binding is also dependent on the plasma concentration of the alpha-1-acid-glycoprotein.

Lidocaine crosses the blood brain and placental barriers, presumably by passive diffusion.

Studies of lidocaine metabolism following intravenous bolus injections have shown that the elimination half-life of this agent is typically 1.5 to 2 hours. Because of the rapid rate at which lidocaine is metabolized, any condition that affects liver function may alter lidocaine kinetics. The half-life may be prolonged two-fold or more in patients with liver dysfunction. Renal dysfunction does not affect lidocaine kinetics but may increase the accumulation of metabolites.

Factors such as acidosis and the use of CNS stimulants and depressants affect the CNS levels of lidocaine required to produce overt systemic effects. Objective adverse manifestations become increasingly apparent with increasing venous plasma levels above 6 g free base per mL. In the rhesus monkey, arterial blood levels of 18-21g/mL have been shown to be threshold for convulsive activity.

INDICATIONS

For the temporary relief of pain and itching associated with minor burns, sunburn, minor cuts, scrapes, insect bites, and minor skin irritation.

CONTRAINDICATIONS

Product should not be used in patients with a history of sensitivity to any of its ingredients or adverse reactions to lidocaine or amide anesthetics, which usually do not cross-react with "caine" ester type anesthetics. If excessive irritation and significant worsening occur, discontinue use and seek the advice of your physician. Product and topical lidocaine should be used cautiously in those with impaired liver function, as well as the very ill or very elderly and those with significant liver disease. Product should be used with caution in patients receiving antiarrhythmic drugs of Class I since the adverse effects are additive and generally synergistic. Product is contraindicated for tuberculous or fungal lesions of skin vaccinia, varicella and acute herpes simplex.

WARNINGS

For external use only. Not for ophthalmic use.

Keep out of reach of children.

Methemoglobinemia

Cases of methemoglobinemia have been reported in association with local anesthetic use. Although all patients are at risk for methemoglobinemia, patients with glucose-6-phosphate dehydrogenase deficiency, congenital or idiopathic methemoglobinemia, cardiac or pulmonary compromise, infants under 6 months of age, and concurrent exposure to oxidizing agents or their metabolites are more susceptible to developing clinical manifestations of the condition. If local anesthetics must be used in these patients, close monitoring for symptoms and signs of methemoglobinemia is recommended.

Signs and symptoms of methemoglobinemia may occur immediately or may be delayed some hours after exposure and are characterized by a cyanotic skin discoloration and abnormal coloration of the blood. Methemoglobin levels may continue to rise; therefore, immediate treatment is required to avert more serious central nervous system and cardiovascular adverse effects, including seizures, coma, arrhythmias, and death.

Discontinue [the use of this product] and any other oxidizing agents. Depending on the severity of the symptoms, patients may respond to supportive care, i.e., oxygen therapy, hydration. More severe symptoms may require treatment with methylene blue, exchange transfusion, or hyperbaric oxygen.

DRUG INTERACTIONS

Patients that are administered local anesthetics may be at increased risk of developing methemoglobinemia when concurrently exposed to the following oxidizing agents:

Class | Examples
Nitrates/Nitrites | nitric oxide, nitroglycerin, nitroprusside, nitrous oxide
Local anesthetics | Articaine, benzocaine, bupivacaine, lidocaine, mepivacaine, prilocaine, procaine, ropivacaine, tetracaine
Antineoplastic agents | cyclophosphamide, flutamide, hydroxyurea, ifosfamide, rasburicase
Antibiotics | dapsone, nitrofurantoin, para-aminosalicylic acid sulfonamides
Antimalarials | chloroquine, primaquine
Anticonvulsants | Phenobarbital, phenytoin, sodium valproate
Other drugs | acetaminophen, metoclopramide, quinine, sulfa drugs (i.e., sulfasalazine)

PATIENT COUNSELING INFORMATION

Inform patients that use of local anesthetics may cause methemoglobinemia, a serious condition that must be treated promptly. Advise patients or caregivers to stop use and seek immediate medical attention if they or someone in their care experience the following signs or symptoms: pale, gray, or blue colored skin (cyanosis); headache; rapid heart rate; shortness of breath; lightheadedness; or fatigue.

Topical formulations of lidocaine may be absorbed to a greater extent through mucous membranes and abraded, fissured or irritated skin than through intact skin. Product should not be ingested or applied into the mouth, inside of the nose or in the eyes. Product should not be used in the ears. Any situation where lidocaine penetrates beyond the tympanic membrane into the middle ear is contraindicated because of ototoxicity associated with lidocaine observed in animals when instilled in the middle ear. Product should not come into contact with the eye or be applied into the eye because of the risk of severe eye irritation and the loss of eye surface sensation, which reduces protective reflexes and can lead to corneal irritation and possibly abrasion. If eye contact occurs, rinse out the eye immediately with saline or water and protect the eye surface until sensation is restored.

PRECAUTIONS

If irritation or sensitivity occurs or infection appears, discontinue use and institute appropriate therapy. If extensive areas are treated, the possibility of systemic absorption exists. Trilocaine™ 4.12% Cream should be used with caution in ill, elderly, debilitated patients and children who may be more sensitive to the systemic effects of lidocaine.

CARCINOGENESIS, MUTAGENESIS AND IMPAIRMENT OF FERTILITY

Studies of lidocaine in animals to evaluate the carcinogenic and mutagenic potential of the effect on fertility have not been conducted.

USE IN PREGNANCY

Teratogenic Effects

Pregnancy Category B

Reproduction studies have been performed for lidocaine in rats at doses up to 6.6 times the human dose and have revealed no evidence of harm to the fetus caused by lidocaine. There are, however, no adequate and well-controlled studies in pregnant women. Animal reproduction studies are not always predictive of human response. General consideration should be given to this fact before administering lidocaine to women of childbearing potential, especially during early pregnancy when maximum organogenesis takes place.

NURSINIG MOTHERS

Lidocaine is excreted in human milk. The clinical significance of this observation is unknown. Caution should be exercised when lidocaine is administered to a nursing woman.

PEDIATRIC USE

Safety and efficacy in children have not been established.

ADVERSE REACTIONS

During or immediately after treatment, the skin at the site of treatment may develop erythema or edema or may be the locus of abnormal sensation.

To report SUSPECTED ADVERSE REACTIONS, contact Trifluent Pharma at (210) 944-6920 or the FDA at 1-800-FDA-1088 or www.fda.gov/medwatch for voluntary reporting of adverse reactions.

DOSAGE AND ADMINISTRATION

Apply a thin film to the affected area two or three times daily or as directed by a physician.

HOW SUPPLIED

Trilocaine™4.12% Cream: 1 oz. (28.3 g) tube - NDC 73352-610-01

STORAGE AND HANDLING

KEEP THIS AND ALL MEDICATIONS OUT OF REACH OF CHILDREN.

Store at 20°-25°C (68°-77°F) [see USP Controlled Room Temperature]. Protect from freezing.

Manufactured in the USA for:
Trifluent Pharma
San Antonio, TX 78213

Trilocaine™

Rev 05/2024

PRINCIPAL DISPLAY PANEL - 28.3 g Tube Pouch Label

NDC: 73352-610-01

Rx only

TRIFLUENT
PHARMA™

Trilocaine™
(4.12% Lidocaine HCl Cream)
Topical Anesthetic
Net Wt. 1 oz. (28.3 g)

Active ingredient: Lidocaine HCl, USP 4.12%

Inactive ingredients: Alkyl (C12-15) benzoate, butylparaben, Carica papaya (papaya) fruit extract,
Carthamus tinctorius (safflower) seed oil, cetyl alcohol, dimethicone, disodium EDTA, emulsifying wax,
ethylparaben, glycerin, glycerol stearate, hydroxypropyl cellulose, isobutylparaben, Lavandula
angustifolia (lavender) oil, methylparaben, PEG 100 stearate, phenoxyethanol, propylene glycol,
propylparaben, purified water, sodium lactate, xanthan gum.

Indications: For the temporary relief of pain and itching associated with minor burns, sunburn, minor
cuts, scrapes, insect bites, and minor skin irritation.

KEEP THIS AND ALL MEDICATIONS OUT OF REACH OF CHILDREN

Usual Adult Dosage: Apply a thin film to the affected area two or three times daily or as directed by a
physician.

Additional Product Information Enclosed.

Caution: For external use only. Not for ophthalmic use.

Store at 20°-25°C (68°-77°F)
[see USP Controlled Room Temperature]. Protect from freezing.

Distributed By:
Trifulent Pharma
San Antonio, TX 78213

610-01
Rev. 03/2024

FPO
Data Matrix